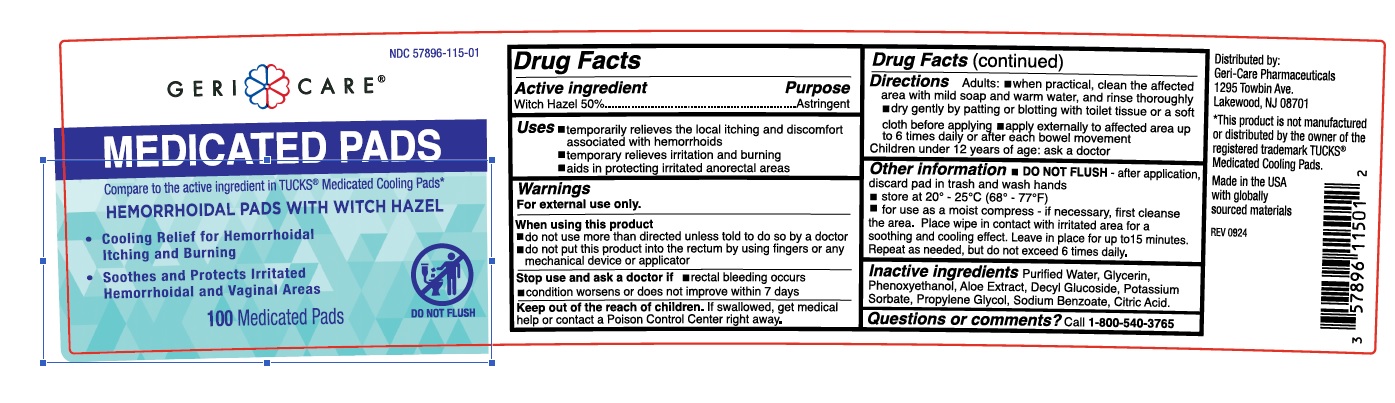 DRUG LABEL: Geri Care Medicated Pads
NDC: 57896-115 | Form: PATCH
Manufacturer: Geri-Care Pharmaceuticals, Corp
Category: otc | Type: HUMAN OTC DRUG LABEL
Date: 20251219

ACTIVE INGREDIENTS: WITCH HAZEL 50 mg/1 mL
INACTIVE INGREDIENTS: ALOE; POTASSIUM SORBATE; SODIUM BENZOATE; PROPYLENE GLYCOL; CITRIC ACID MONOHYDRATE; WATER; PHENOXYETHANOL; DECYL GLUCOSIDE; GLYCERIN

Geri Care Medicated Pads

Active Ingredient

Witch Hazel 50%

Purpose Section

Astringent

Uses

- temporary relieves the local ithcing and discomfort associated with hemmorhoids
- temporary relieves irritation and burning
- aids in protecting irritated anorectal areas

Warnings

For external use only

When using this product

- do not use more than directed unless told to do so by a doctor
  - do no put this product into the rectum by using fingers or any mechanical device or applicator

Stop use and ask a doctor if

- rectal bleeding occurs
- condition worsens or does not improve within 7 days

Keep out of the reach of children

If swallowed, get medical help or contact a Poison Control Center right away

Directions

Adults

- when practical, clean the affected area with mild soap and warm water, and rinse thoroughly
- dry gently by patting or blotting with toilet tissue or a soft cloth before applying
- apply externally to affected areas upto 6 times daily or after each bowel movement

Children under 12 years of age: Ask a doctor

Other Information

- DO NOT FLUSH - after application, discard pad in thrash and wash hands
- store at 20º - 25ºC (68º - 77ºF)
  - for use as a mosit compress - if necessary, first cleanse the area. Place wipe in contact with irritated area for a soothing and cooling effect. Leave in place for upto 15 minutes. Repeat as needed, but do not exceed 6 times daily.

Inactive Ingredients

Purified Water, Glycerin, Phenoxyethanol, Aloe Extract, Decyl Glucoside, Potassium Sorbate, Propylene Glycol, Sodium Benzoate, Citric Acid

Questions or Comments

Call 1-800-540-3765

Principal Display Panel

NDC: 57896-115-01

GERI CARE

MEDICATED PADS
Compare to the active ingredients in TUCKS® Medicated Cooling Pads*

HEMORRHOIDAL PADS WITH WITCH HAZEL

- Cooling Relief for Hemorrhoidal Itching and Burning
  - Soothes and Protects Irritated Hemorrhoidal and Vaginal Areas

100 Medicated Pads

DO NOT FLUSH